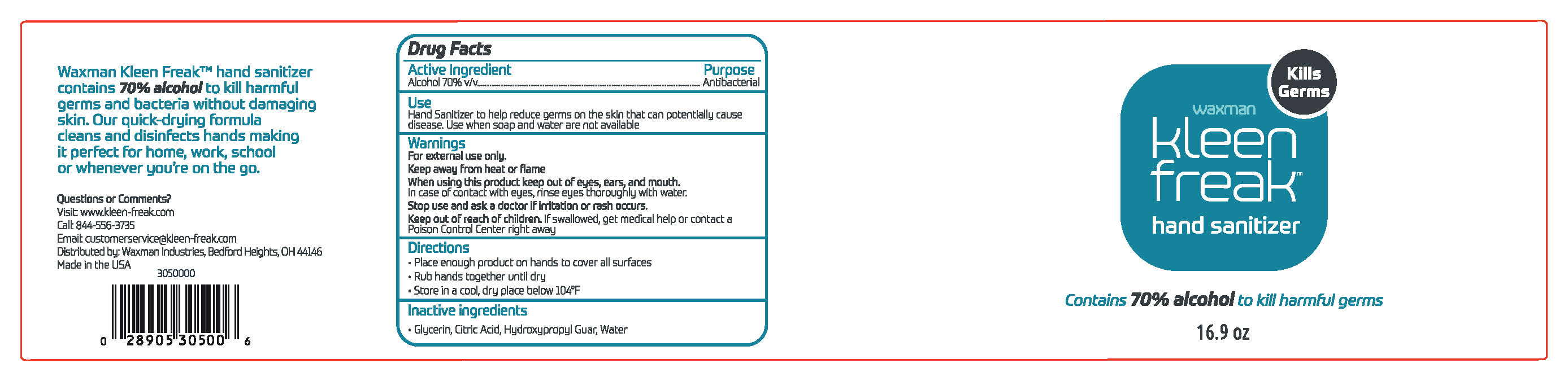 DRUG LABEL: Waxman Kleen Freak Hand Sanitizer
NDC: 74299-371 | Form: LIQUID
Manufacturer: Southern Distilling Company, LLC
Category: otc | Type: HUMAN OTC DRUG LABEL
Date: 20200801

ACTIVE INGREDIENTS: ALCOHOL 0.62 mL/1 mL
INACTIVE INGREDIENTS: WATER; ANHYDROUS CITRIC ACID; GLYCERIN; HYDROXYPROPYL GUAR (2500-4500 MPA.S AT 1%)

Active ingredient

Alcohol 70% v/v. Purpose: Antiseptic

Purpose

Antiseptic, Hand Sanitizer

Use

Hand Sanitizer to help reduce germs on the skin that potentially can cause disease. Use when soap and water are not available.

Warnings

For external use only. Flammable. Keep away from heat or flame.

When using this product keep out of eyes, ears, and mouth. In case of contact with eyes, rinse eyes thoroughly with water.

Stop use and ask a doctor if irritation or rash occurs.

Keep out of reach of children. If swallowed, get medical help or contact a Poison Control Center right away.

Directions

- Place enough product on hands to cover all surfaces.
- Rub hands together until dry

STORAGE AND HANDLING

- Store in a cool, dry place below 104F

Inactive ingredients

Glycerin, Citric Acid, Hydroxypropyl Guar, Water